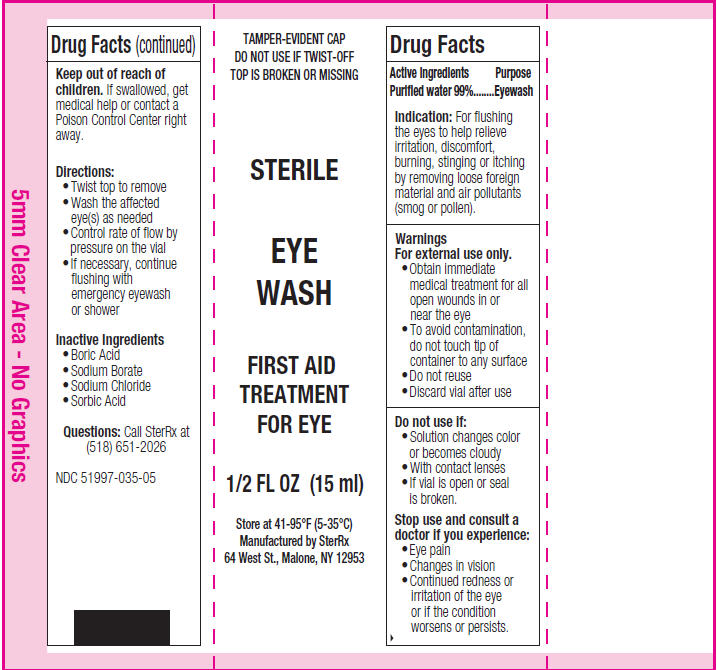 DRUG LABEL: Emergency Eye Wash, PW, Sterile 
NDC: 51997-035 | Form: FOR SOLUTION
Manufacturer: Asept Pak, Inc.
Category: otc | Type: HUMAN OTC DRUG LABEL
Date: 20120827

ACTIVE INGREDIENTS: Water 14.85 mL/15 mL
INACTIVE INGREDIENTS: Boric Acid; Sodium Borate; Sodium Chloride; Sorbic Acid

Emergency Eye Wash, PW, Sterile 15 ml
Ster-Aide

Drug Facts

Active Ingredients

Purified water 99%

Purpose

Eyewash

Indication

For flushing the eyes to help relieve irritation, discomfort, burning, stinging or itching by removing loose foreign material and air pollutants (smog or pollen).

Warnings

WHEN USING

For external use only.

- Obtain immediate medical treatment for all open wounds in or near the eye
- To avoid contamination, do not touch tip of container to any surface
- Do not reuse
- Discard vial after use

Do not use if:

- Solution changes color or becomes cloudy
- With contact lenses
- If vial is open or seal is broken.

Stop use and consult a doctor if you experience:

- Eye pain
- Changes in vision
- Continued redness or irritation of the eye or if the condition worsens or persists.

Keep out of reach of children. If swallowed, get medical help or contact a Poison Control Center right away.

Directions

- Twist top to remove
- Wash the affected eye(s) as needed
- Control rate of flow by pressure on the vial
- If necessary, continue flushing with emergency eyewash or shower

Inactive Ingredients

- Boric Acid
- Sodium Borate
- Sodium Chloride
- Sorbic Acid

Questions

Call SterRx at (518) 651-2026

NDC 51997-035-05

STORAGE AND HANDLING

Store at 41-95°F (5-35°C)

Manufactured by SterRx
64 West St., Malone, NY 12953

PRINCIPAL DISPLAY PANEL - 15 ml Vial Label

TAMPER-EVIDENT CAP
DO NOT USE IF TWIST-OFF
TOP IS BROKEN OR MISSING

STERILE

EYE
WASH

FIRST AID
TREATMENT
FOR EYE

1/2 FL OZ (15 ml)

Store at 41-95°F (5-35°C)
Manufactured by SterRx
64 West St., Malone, NY 12953